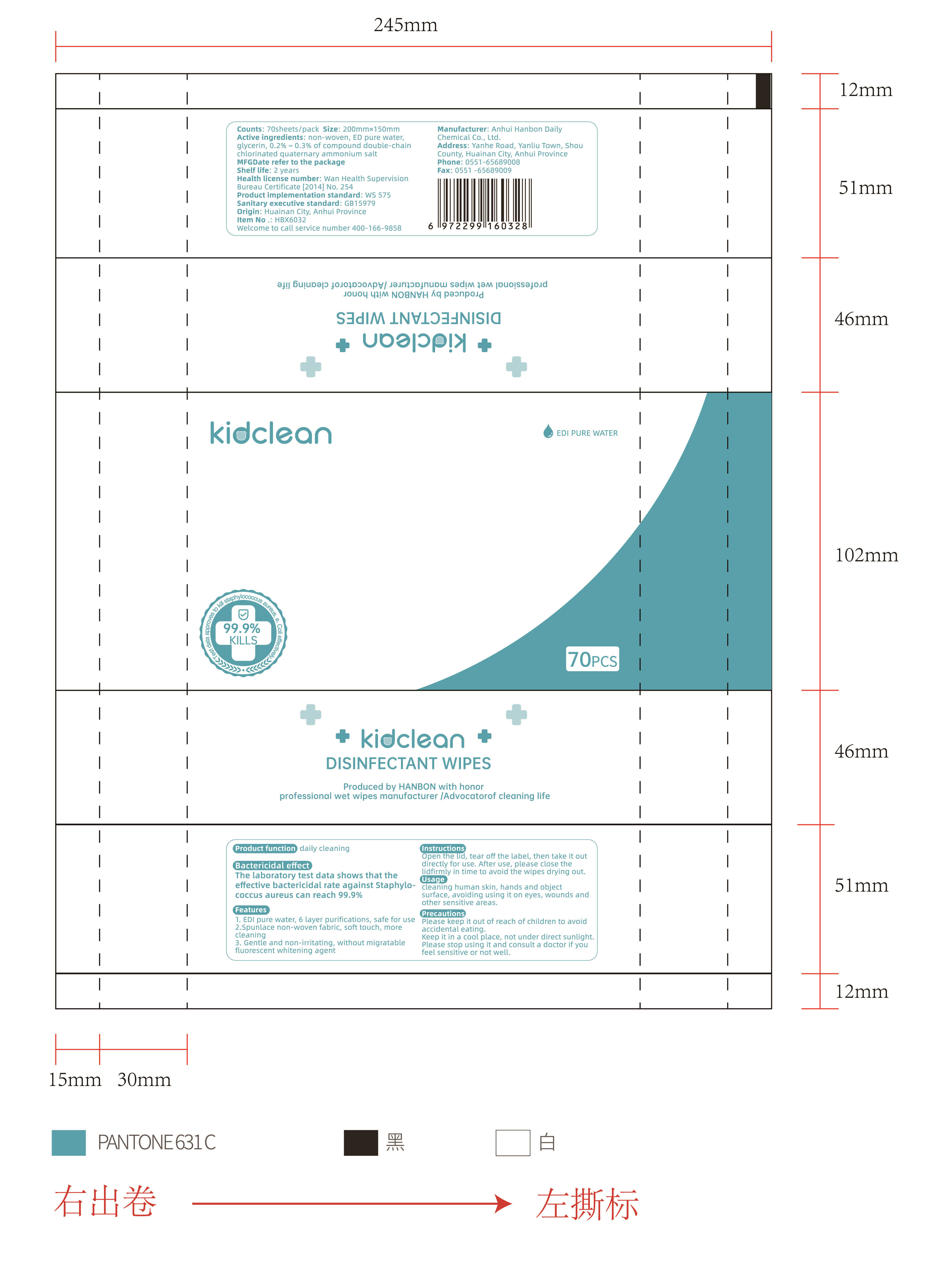 DRUG LABEL: Wet Wipes
NDC: 40562-006 | Form: CLOTH
Manufacturer: Anhui Hanbon Daily Chemical Co., Ltd.
Category: otc | Type: HUMAN OTC DRUG LABEL
Date: 20200422

ACTIVE INGREDIENTS: GLYCERIN 0.21 1/70 1
INACTIVE INGREDIENTS: TEA TREE OIL; CHAMOMILE; ALOE VERA LEAF; WATER; N-ALKYL ETHYLBENZYL DIMETHYL AMMONIUM CHLORIDE (C12-C14); ANHYDROUS CITRIC ACID; BENZALKONIUM CHLORIDE; DIDECYLDIMONIUM CHLORIDE; PROPYLENE GLYCOL

ACTIVE INGREDIENT

Glycerol

PURPOSE

Disinfection
Sterilization
No Rinseing

WARNINGS

Open the lid, tear off the label, then take it out directly for use. After use, please close the
lidfirmly in time to avoid the wipes drying out.

DOSAGE AND ADMINISTRATION

Please keep it out of reach of children to avoid accidental eating.
Keep it in a cool place, not under direct sunlight.
Please stop using it and consult a doctor if you feel sensitive or not well.

keep out of reach of children

INACTIVE INGREDIENT

Deionized water,propylene glycol,Aloe Barbadensis Leaf Extract,Benzalkonium chloride,Chamomilla recutita flower extract,Didecyldimonium Chloride,C12-14 alkyl dimethyl ethylbenzyl ammonium chloride,Tea tree oil,Citric Acid

INDICATIONS AND USAGE

cleaning human skin, hands and object surface, avoiding using it on eyes, wounds and other sensitive areas.